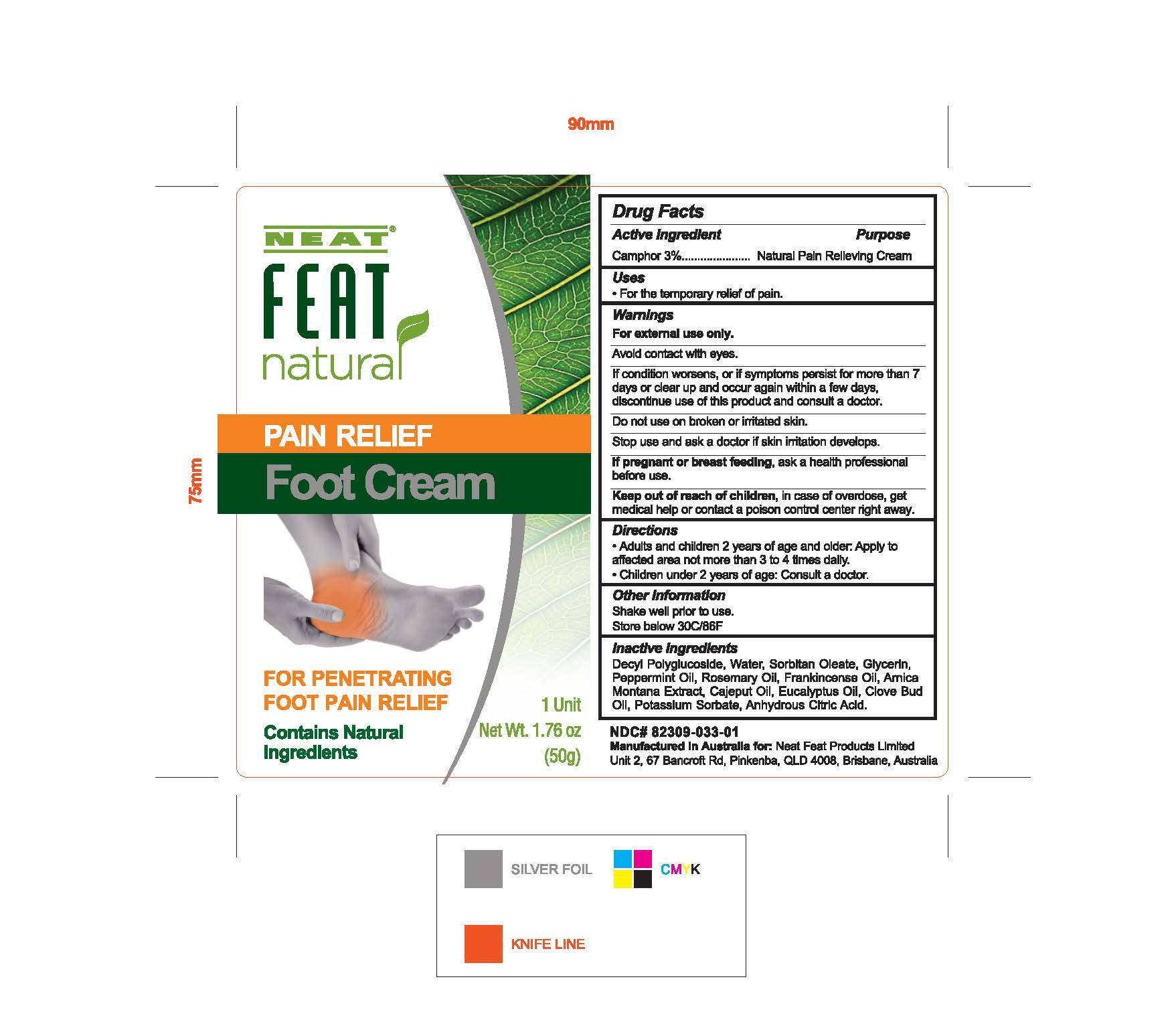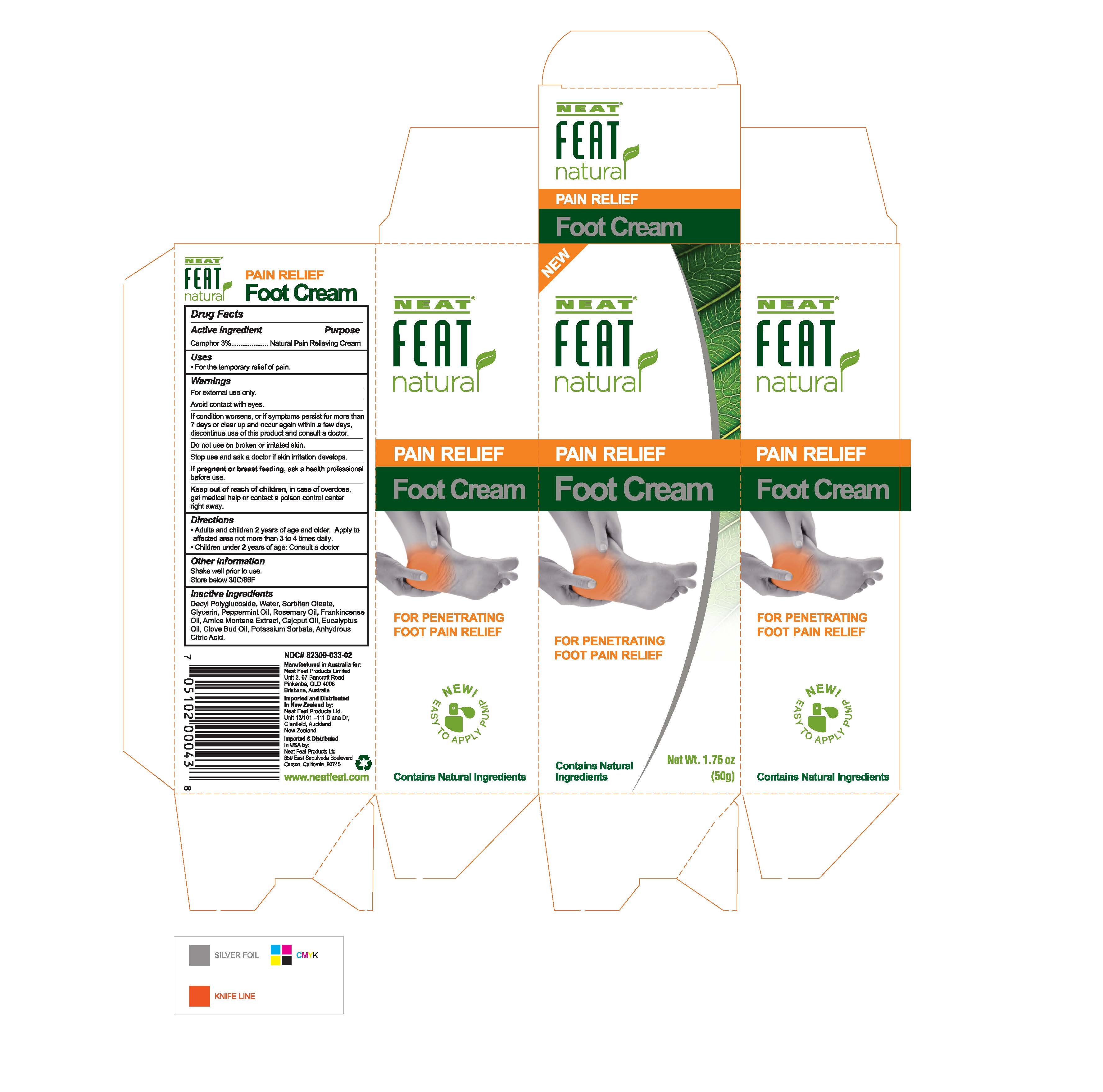 DRUG LABEL: Natural Pain Relief Foot Cream
NDC: 82309-033 | Form: CREAM
Manufacturer: Tripak Pharmaceuticals
Category: otc | Type: HUMAN OTC DRUG LABEL
Date: 20231218

ACTIVE INGREDIENTS: CAMPHOR (NATURAL) 1.5 g/50 g
INACTIVE INGREDIENTS: PEG-6 SORBITAN OLEATE; GLYCERIN; ROSEMARY OIL; EUCALYPTUS OIL; POTASSIUM SORBATE; ANHYDROUS CITRIC ACID; WATER; DECYL GLUCOSIDE; PEPPERMINT OIL; FRANKINCENSE OIL; ARNICA MONTANA; CAJUPUT OIL; CLOVE OIL

Pain Relief Foot Cream

Active Ingredient

Active Ingredient Purpose

Camphor 3%..............................................................................Pain Relieving cream

Purpose

Natural Pain Relieving Cream

Uses

- For the temporary relief of pain.

Warnings

For external use only.

_____________________________________

Avoid contact with eyes.

_____________________________________

If condition worsens, or if symptoms persist for more than 7 days or clear up and occur agai within a few days, discontinue use of this product and consult a doctor.

Do not use on broken or irritated skin.

Stop Use

Stop use and ask a doctor if skin irritation develops.

If pregnant or breastfeeding, ask a health professional before use.

Keep out of reach of children, in case of overdose, get medical help or contact a poison control center right away.

Directions

- Adults and children 2 years of age and older: Apply to affected area not more than 3 to 4 times daily.
- Children under 2 years of age: Consult a doctor.

Other Information

Shake well prior to use.

Store below 30C/86F

Inactive Ingredients

Arnica montana extract, Anhydrous citric acid, frankincense oil, cajuput oil, camphor (natural) decyl glucoside, citric acid, clove oil, decyl polyglucoside, eucalyptus oil, glycerin, peppermint oil, potassium sorbate, purified water, sorbitan oleate, rosemary oil

Natural Foot Cream Box

Label 82309-033-01

Label

82309-33-02 Box